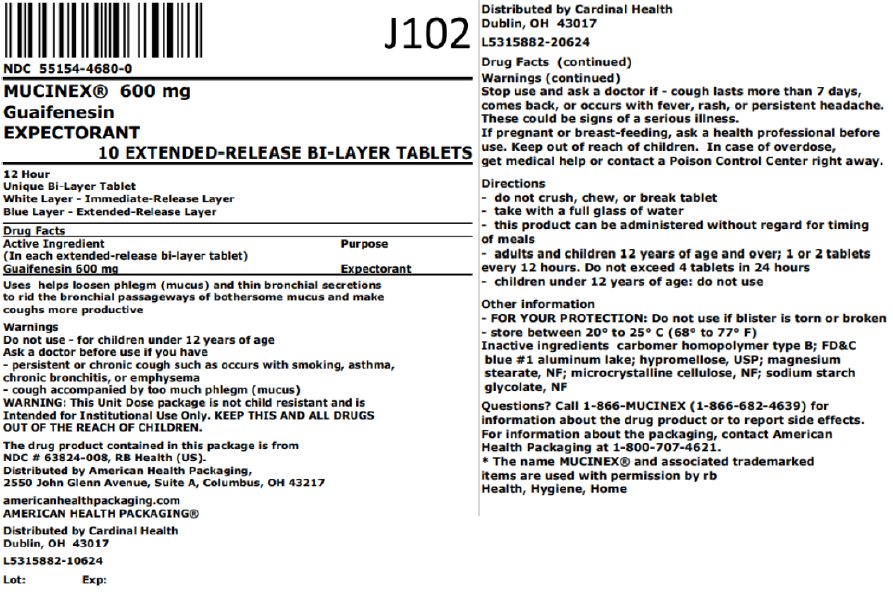 DRUG LABEL: Mucinex
NDC: 55154-4680 | Form: TABLET, EXTENDED RELEASE
Manufacturer: Cardinal Health 107, LLC
Category: otc | Type: HUMAN OTC DRUG LABEL
Date: 20251010

ACTIVE INGREDIENTS: GUAIFENESIN 600 mg/1 1
INACTIVE INGREDIENTS: CARBOMER HOMOPOLYMER TYPE B (ALLYL PENTAERYTHRITOL CROSSLINKED); FD&C BLUE NO. 1 ALUMINUM LAKE; HYPROMELLOSE, UNSPECIFIED; MAGNESIUM STEARATE; MICROCRYSTALLINE CELLULOSE; SODIUM STARCH GLYCOLATE TYPE A POTATO

Mucinex ®

Drug Facts

Active ingredient (in each extended-release bi-layer tablet)

Guaifenesin 600 mg

Purpose

Expectorant

Uses

helps loosen phlegm (mucus) and thin bronchial secretions to rid the bronchial passageways of bothersome mucus and make coughs more productive

Warnings

Do not use

- for children under 12 years of age

Ask a doctor before use if you have

- persistent or chronic cough such as occurs with smoking, asthma, chronic bronchitis, or emphysema
- cough accompanied by too much phlegm (mucus)

Stop use and ask a doctor if

- cough lasts more than 7 days, comes back, or occurs with fever, rash, or persistent headache. These could be signs of a serious illness.

PREGNANCY OR BREAST FEEDING

If pregnant or breast-feeding, ask a health professional before use.

Keep out of reach of children. In case of overdose, get medical help or contact a Poison Control Center right away.

Directions

- do not crush, chew, or break tablet
- take with a full glass of water
- this product can be administered without regard for the timing of meals
- adults and children 12 years of age and over: 1 or 2 tablets every 12 hours. Do not exceed 4 tablets in 24 hours.
- children under 12 years of age: do not use

Other information

- FOR YOUR PROTECTION: Do not use if blister is torn or broken.
- store between 20-25°C (68-77°F)

Inactive ingredients

carbomer homopolymer type B; FD&C blue #1 aluminum lake; hypromellose, USP; magnesium stearate, NF; microcrystalline cellulose, NF; sodium starch glycolate, NF

Questions?

1-866-MUCINEX (1-866-682-4639) for information about the drug product or to report side effects. For information about packaging, contact American Health Packaging at 1-800-707-4621.

*The name MUCINEX ® and associated trademarked items are used with permission by Reckitt Benckiser

The drug product contained in this package is originally from Reckitt Benckiser.

Packaged and Distributed by American Health Packaging, 2550 John Glenn Avenue, Suite A, Columbus, OH 43217

Overbagged with 10 extended-release (bi-layer) tablets per bag, NDC 55154-4680-0

Distributed By:

Cardinal Health

Dublin, OH 43017

L5315882-10624 / L5315882-20624

057201
5500408/0915

Principal Display Panel

NDC 55154-4680-0

MUCINEX® 600mg

Guaifenesin

EXPECTORANT

10 EXTENDED-RELEASE BI-LAYER TABLETS